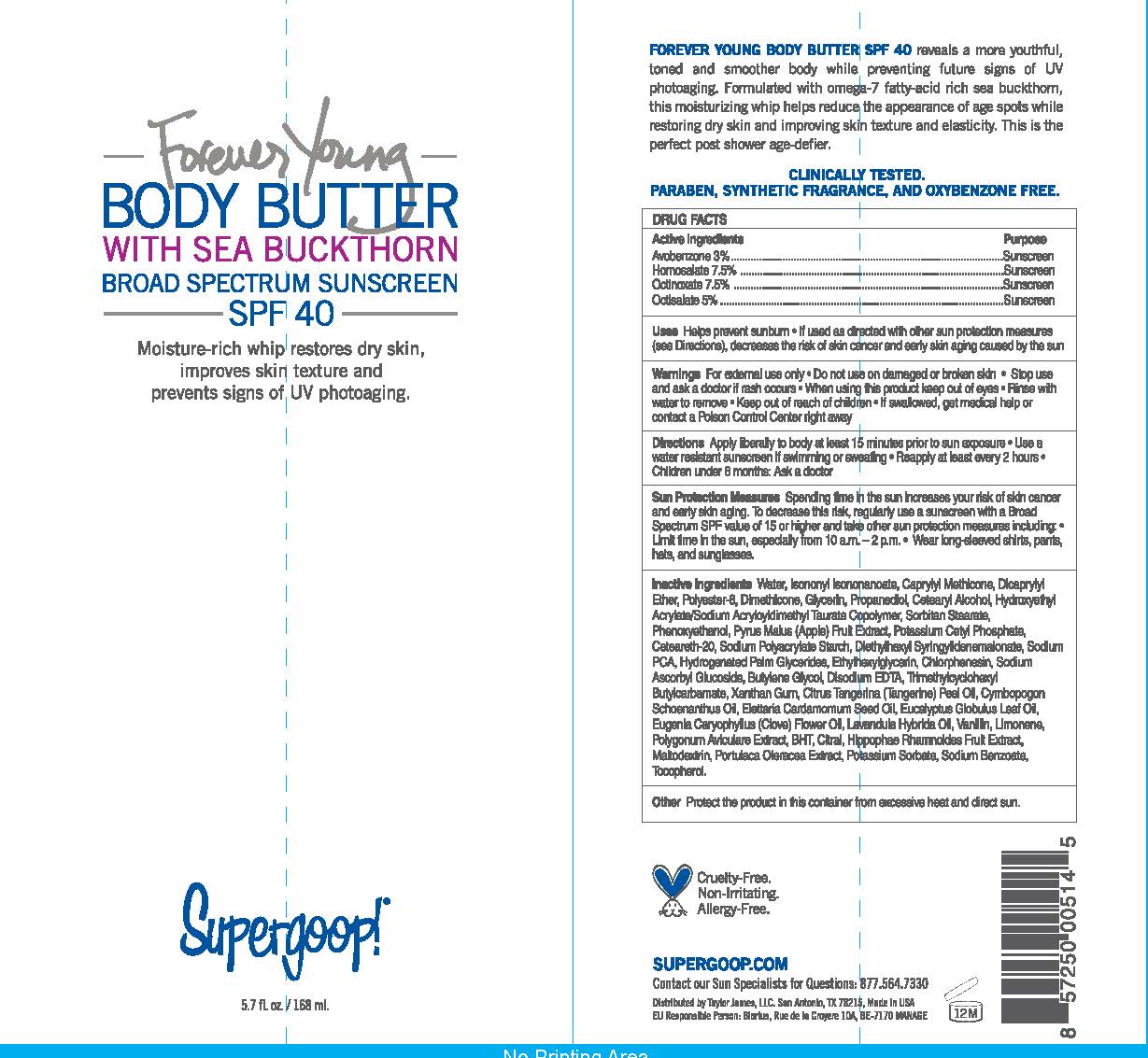 DRUG LABEL: Forever Young Body Butter Broad Spectrum Sunscreen SPF 40

NDC: 75936-139 | Form: CREAM
Manufacturer: Taylor James Ltd
Category: otc | Type: HUMAN OTC DRUG LABEL
Date: 20201112

ACTIVE INGREDIENTS: AVOBENZONE 3 g/100 mL; HOMOSALATE 7.5 g/100 mL; OCTINOXATE 7.5 g/100 mL; OCTISALATE 5 g/100 mL
INACTIVE INGREDIENTS: WATER; ISONONYL ISONONANOATE; CAPRYLYL TRISILOXANE; DICAPRYLYL ETHER; POLYESTER-8 (1400 MW, CYANODIPHENYLPROPENOYL CAPPED); DIMETHICONE; GLYCERIN; PROPANEDIOL; CETOSTEARYL ALCOHOL; HYDROXYETHYL ACRYLATE/SODIUM ACRYLOYLDIMETHYL TAURATE COPOLYMER (45000 MPA.S AT 1%); SORBITAN MONOSTEARATE; PHENOXYETHANOL; APPLE; POTASSIUM CETYL PHOSPHATE; POLYOXYL 20 CETOSTEARYL ETHER; SODIUM POLYACRYLATE (8000 MW); STARCH, CORN; DIETHYLHEXYL SYRINGYLIDENEMALONATE; SODIUM PYRROLIDONE CARBOXYLATE; HYDROGENATED PALM GLYCERIDES; ETHYLHEXYLGLYCERIN; CHLORPHENESIN; BUTYLENE GLYCOL; EDETATE DISODIUM; XANTHAN GUM; MANDARIN OIL; CYMBOPOGON SCHOENANTHUS OIL; CARDAMOM OIL; EUCALYPTUS OIL; CLOVE OIL; LAVANDIN OIL; VANILLA; LIMONENE, (+)-; POLYGONUM AVICULARE TOP; BUTYLATED HYDROXYTOLUENE; HIPPOPHAE RHAMNOIDES FRUIT; MALTODEXTRIN; PURSLANE; POTASSIUM SORBATE; SODIUM BENZOATE; TOCOPHEROL

Forever Young Body Butter

Active Ingredient ................. Purpose

Avobenzone 3 % ................ Sunscreen

Homosalat 7.5 %................ Sunscreen

Otinoxate 7.5% ................ Sunscreen

Octisalate 5% ................ Sunscreen

Uses

Helps prevent sunburn

If used as directed with other sun protection measures (see Directions), decreases the risk of skin cancer and early skin aging caused by the sun

Keep out of reach of children

Stop use and ask a doctor if rash occurs

WARNINGS

For external use only

Do not use on damaged or broken skin

When using this prodcut keep out of eyes

Rinse with water to remove

If swallowed, get medical help or contact a Poison Control Center right away

Directions

Apply Liberally to body at least 15 minutes prior to sune exposure

Use a water resistant sunscreen if swimming or sweating

Reapply at least every 2 hours

Children under 6 months: Ask a doctor

Sun Protection Measures

Spending time in the sun increases your risk of skin cancer and early skin aging. To decrease risk, regularly use a sunscreen with a Broad Spectrum SPF value of 15 or higher and take other sun protection measures including:

Limit time in the sun, especially from 10 a.m. - 2 p.m.

Wear long-sleeved shirts, pants, hates, and sunglasses

INACTIVE INGREDIENT

Water, Isononyl Isononanoate, Caprylyl Methicone, Dicaprylyl Ether, Polyester-8, Demthicone, Glycerin, Propanediol, Cetearyl Alcohol, Hydroxyethyl Acrylate/Sodium Acryloyldimethyl Taurate Copolymer, Sorbitan Stearate, Phenoxyethanol, Pyrus Mallus (Apple) Fruit Extract, Potassium Cetyl Phosphate, Ceteareth-20, Sodium Polyactylate, Starch, Diethylhexyl Syringylidenemalonate, Sodium PCA, Hydrogenated Palm Glycerides, Ethylhexyglycerin, Chlorphenesin, Sodium Ascorbyl Glucoside, Butylene Glycol, Disodium EDTA, Trimethylcyclohexyl Butylcarbamate, Xanthan Gum, Citrus Tangerina (Tangerine) Peel Oil, Cymbopogon Shoenanthus Oil, Elettaria Cardamomum Seed Oil, Eucalyptus Globulus Leaf Oil, Eugenia Caryophylus (Clove) Flower Oil, Lavandula Hyrvida Oil, Vanilli, Limonene, Polygonum Aviculare Extract, BHT, Citral, Hippophae Rhamnoides Fruit Extract, Maltodextrin, Portulaca Oleracea Extract, Potassium Sorbate, Sodium Benzoate, Tocopherol.

PACKAGE LABEL

Forever Young

Body Butter

With Sea Buckthorn

Broad Spectrum Sunscreen SPF 40

5.7 fl. oz. /168 ml.